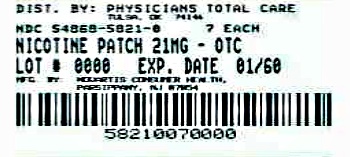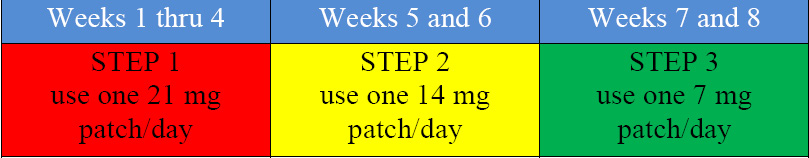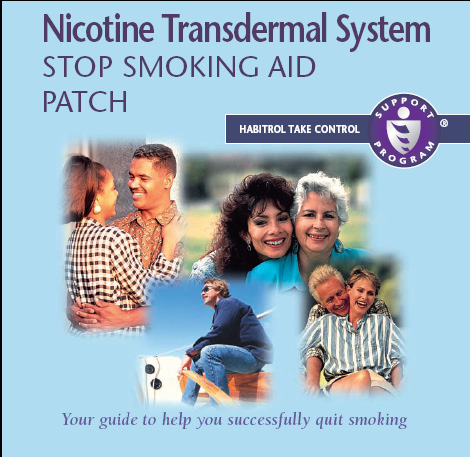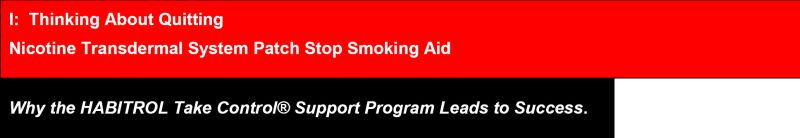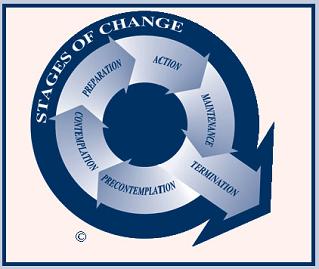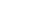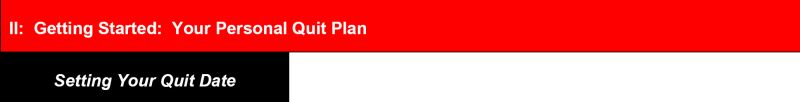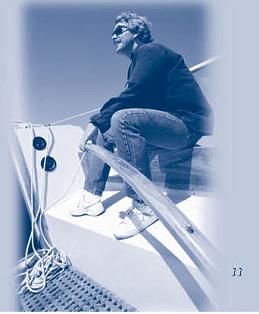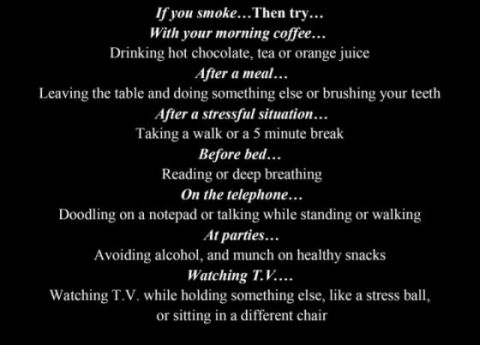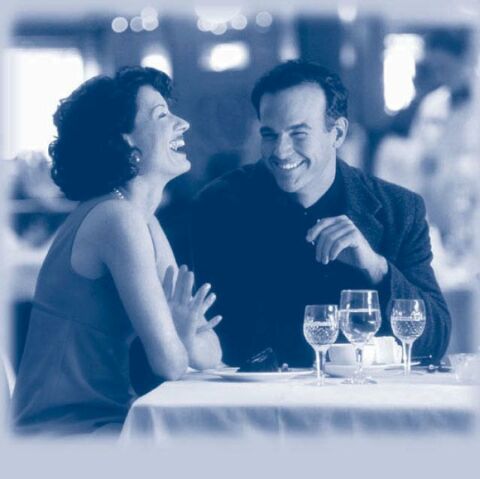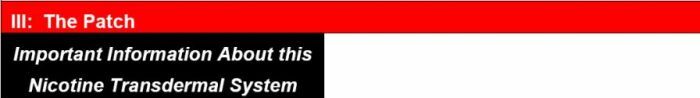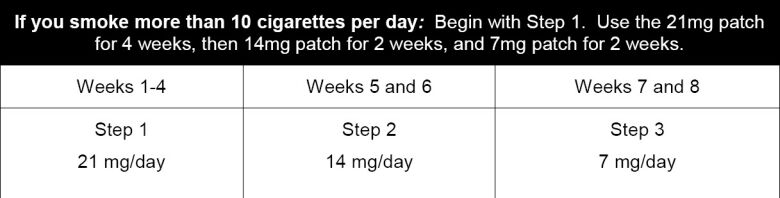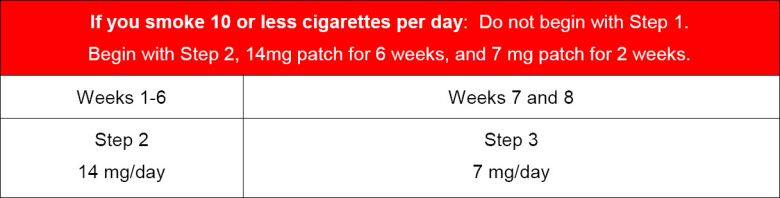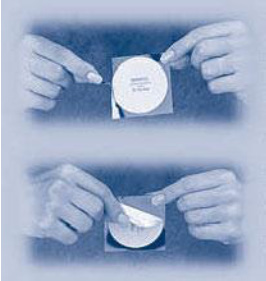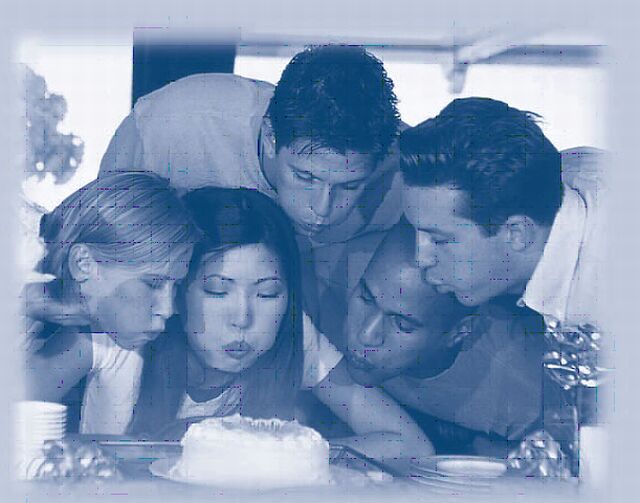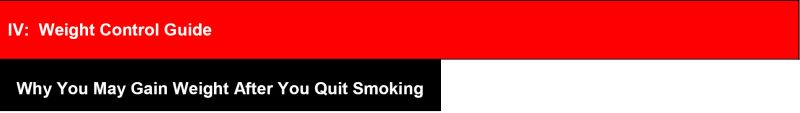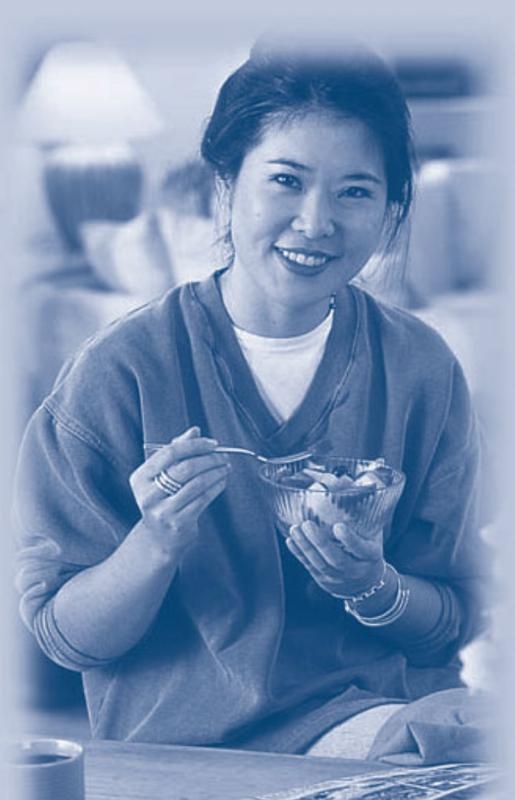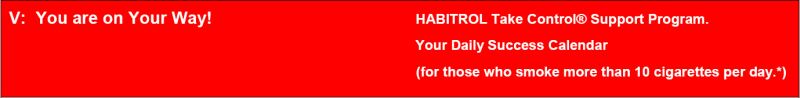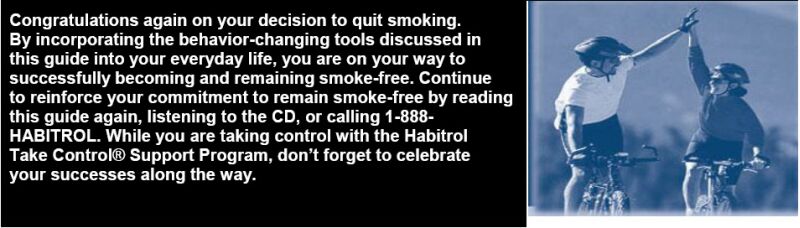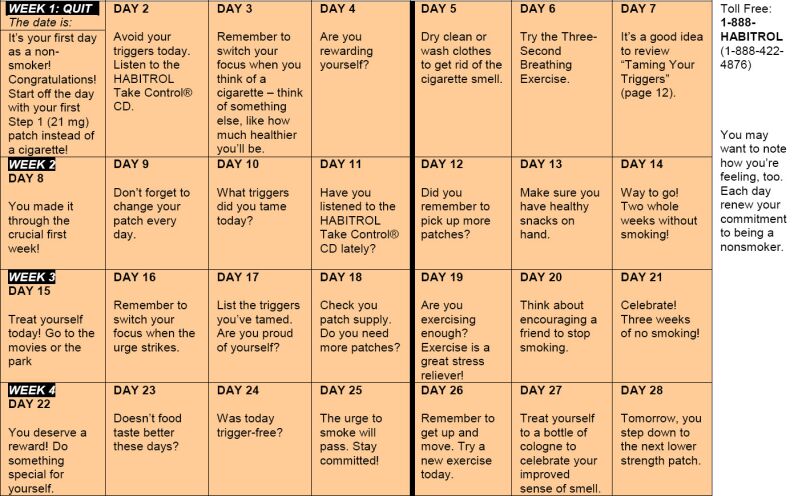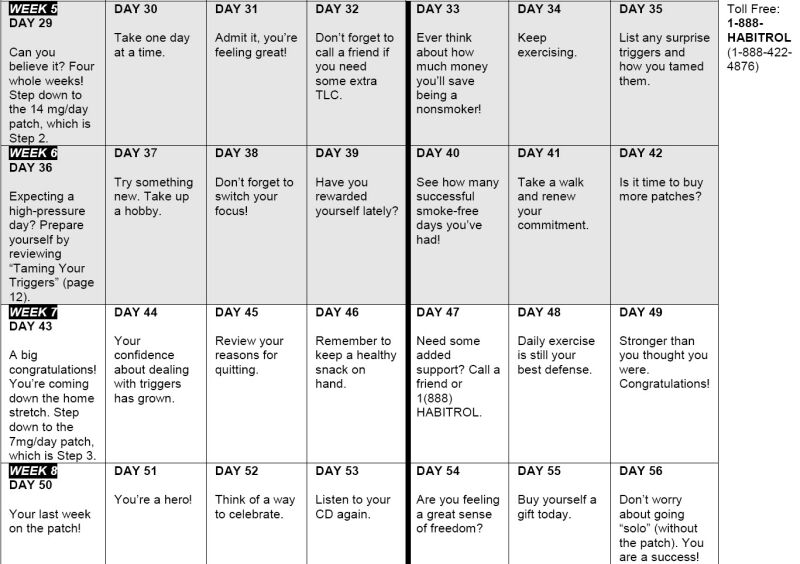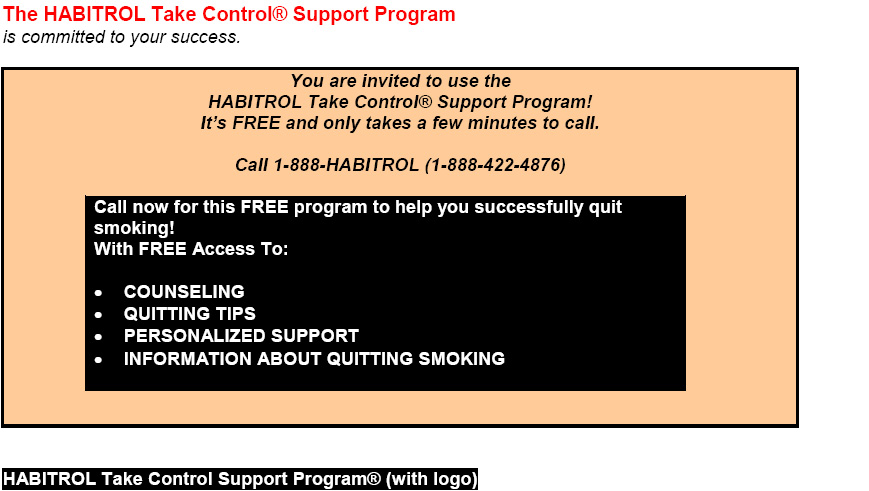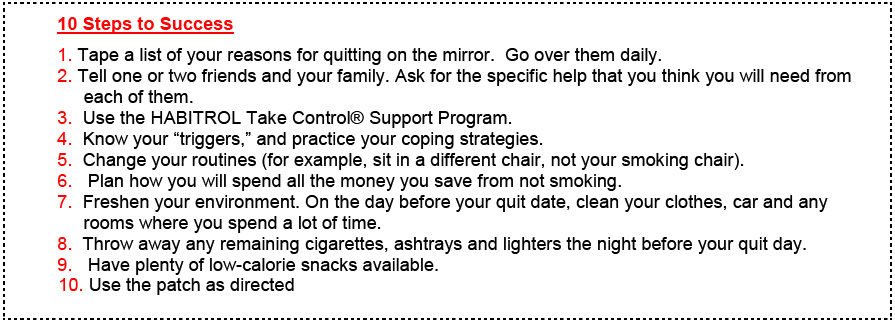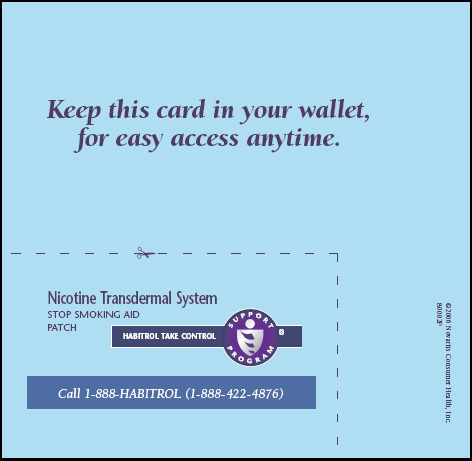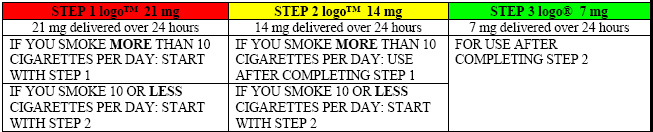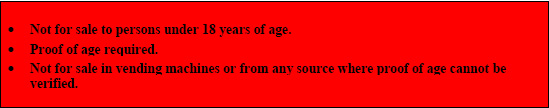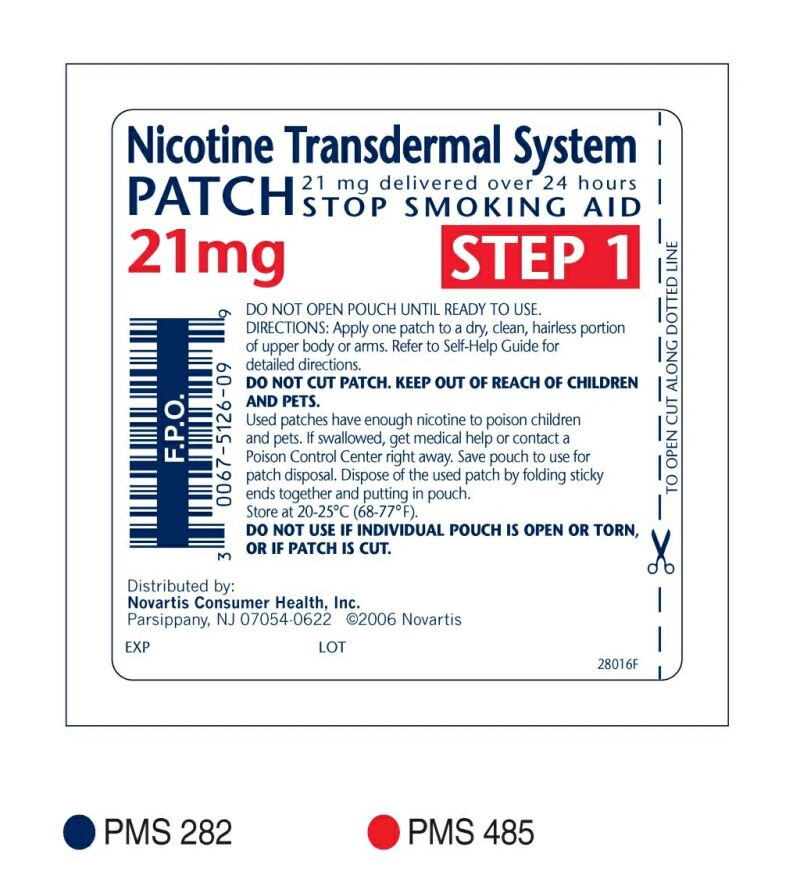 DRUG LABEL: NICOTINE
NDC: 54868-5821 | Form: PATCH, EXTENDED RELEASE
Manufacturer: Physicians Total Care, Inc.
Category: otc | Type: HUMAN OTC DRUG LABEL
Date: 20120522

ACTIVE INGREDIENTS: NICOTINE 21 mg/24 h
INACTIVE INGREDIENTS: METHACRYLIC ACID

Drug Facts

Active ingredient

Nicotine, 21 mg delivered over 24 hours

Purpose

Stop smoking aid

Uses

reduces withdrawal symptoms, including nicotine craving, associated with quitting smoking.

Warnings

If you are pregnant or breast-feeding, only use this medicine on the advice of your health care provider. Smoking can seriously harm your child. Try to stop smoking without using any nicotine replacement medicine. This medicine is believed to be safer than smoking. However, the risks to your child from this medicine are not fully known.

Do not use

- if you continue to smoke, chew tobacco, use snuff, use nicotine gum, or use another nicotine patch or other nicotine containing products

Ask a doctor before use if you have

- heart disease, recent heart attack, or irregular heartbeat. Nicotine can increase your heart rate.
- high blood pressure not controlled with medication. Nicotine can increase your blood pressure.
- an allergy to adhesive tape or have skin problems, because you are more likely to get rashes.

Ask a doctor or pharmacist before use if you are

- using a non-nicotine stop smoking drug
- taking a prescription medicine for depression or asthma. Your prescription dose may need to be adjusted

When using this product

- do not smoke even when not wearing the patch. The nicotine in your skin will still be entering your bloodstream for several hours after you take off the patch.
- if you have vivid dreams or other sleep disturbances remove this patch at bedtime

Stop use and ask a doctor if

- skin redness caused by the patch does not go away after four days, or if your skin swells, or you get a rash
- irregular heartbeat or palpitations occur
- you get symptoms of nicotine overdose, such as nausea, vomiting, dizziness, weakness and rapid heartbeat

Keep out of reach of children and pets

Used patches have enough nicotine to poison children and pets. If swallowed, get medical help or contact a Poison Control Center right away. Save pouch to use for patch disposal. Dispose of the used patches by folding sticky ends together and putting in pouch.

Directions

- If you are under 18 years of age, ask a doctor before use
- before using this product, read the enclosed self-help guide for complete directions and other information
- stop smoking completely when you begin using the patch
- if you smoke more than 10 cigarettes per day, use the following schedule below:

- if you smoke 10 or less cigarettes per day, start with Step 2 for 6 weeks, then Step 3 for 2 weeks and then stop
- apply one new patch every 24 hours on skin that is dry, clean and hairless
- remove backing from patch and immediately press onto skin. Hold for 10 seconds.
- wash hands after applying or removing patch. Save pouch to use for patch disposal. Dispose of the used patches by folding sticky ends together and putting in pouch.
- the used patch should be removed and a new one applied to a different skin site at the same time each day
- if you have vivid dreams, you may remove the patch at bedtime and apply a new one in the morning
- do not wear more than one patch at a time
- do not cut patch in half or into smaller pieces
- do not leave patch on for more than 24 hours because it may irritate your skin and loses strength after 24 hours
- to avoid possible burns, remove patch before undergoing any MRI (magnetic resonance imaging) procedures
- stop using the patch at the end of 8 weeks. If you still feel the need to use the patch talk to your doctor.

Other information

● store at 20-25°C (68-77°F)

USER'S GUIDE

USER’S GUIDE

Nicotine Transdermal System

STOP SMOKING AID PATCH

HABITROL TAKE CONTROL SUPPORT PROGRAM® (with logo)

Your guide to help you successfully quit smoking

Table of Contents

I: Thinking About Quitting

Why the HABITROL Take Control® Support Program Leads to Success ….... 3
Working Towards Success: The Stages of Change ........................................... 5
Which Way Now? ............................................................................................ 8
Why I Want to Stop Smoking ........................................................................... 8
Health Benefits of Quitting ...............................................................................

II: Getting Started: Your Personal Quit Plan

Setting Your Quit Date ..................................................................................... 10

Understanding Nicotine Addiction ................................................................... 10

Smoking and Your Body ................................................................................. 10
Smoking and Your Mind ................................................................................. 11
Knowing Your Triggers ................................................................................... 12

Taming Your Triggers ...................................................................................... 12

Reducing the Urge to Smoke ........................................................................... 12

Building Your Supporting Cast ....................................................................... 14

Countdown to Quit Day: 10 Steps to Success ................................................. 15

Rewarding Yourself ....................................................................................... 16

If You Slip ..................................................................................................... 16

III: The Patch

Important Information About this Nicotine Transdermal System ................... 18

How the Patch Works .................................................................................... 19

How to Use the Patch .................................................................................... 20

IV: Weight Control Guide .......................................................................... 27

V: You Are on Your Way ......................................................................... 29

VI: Your Daily Success Calendar ............................................................. 30

VII: HABITROL Take Control® Support Program Resources ............. 34

Congratulations! You’ve joined millions of others who have made the important and rewarding decision to quit smoking. A large percentage of smokers have already successfully quit. You can too. You’ve already taken the first smart step by choosing the patch and the HABITROL Take Control® Support Program. The program includes the use of nicotine replacement therapy and behavioral support, a combination that can significantly increase your chances of quitting.

The patch helps smokers quit smoking by reducing nicotine withdrawal symptoms. Many patch users will be able to stop smoking for at least a few days, but many will start smoking again. Most smokers usually have to try to quit several times before they completely stop.

Your own chances to stop smoking depend on how strongly you are addicted to nicotine, how much you want to quit, and how closely you follow a quitting program like the one that comes with this product. If you find you cannot stop or if you start smoking again after using this product, please talk to a health care professional who can help you find a program that may work better for you.

First, there is the 3-step nicotine patch that delivers controlled amounts of nicotine to help reduce your withdrawal cravings for nicotine. The patch utilizes nicotine replacement therapy, and through the use of step-down dosing, gradually reduces the amount of nicotine in your system.

Second, the HABITROL Take Control® Support Program, developed by behavioral change and smoking cessation experts, recognizes that quitting smoking is a personal journey that occurs in six stages, known as the “Stages of Change.”

The HABITROL Take Control® Support Program offers the following support elements to help you quit:

1. This guide will teach you how to move through the quit process by helping you to identify your reasons for quitting, manage urges to smoke, recover from slips and control your weight.
2. An optional compact disc* gives you more information about the patch and the six “Stages of Change.” It provides guidance about what to do at each stage to increase your chances of quitting for good, as well as, relaxation techniques to help you become and remain smoke-free. It also includes a full track of soothing instrumental music.
3. 1-888-HABITROL — our toll-free telephone support center, staffed by smoking cessation professionals, will offer you friendly support and information. Call Monday through Friday between 9 a.m. and 8 p.m. ET. You can use this resource to help you get ready to quit, manage urges, cope with withdrawal symptoms, recover from slips and deal with smoking spouses and friends.

*If you need a cassette tape instead of the compact disc, please call 1-888-HABITROL.

Working Towards Success

— The Stages of Change

Quitting smoking is a process that begins long before your quit day. Researchers have determined that smokers go through the following six “Stages of Change” while on the road to becoming smoke-free.

Pre-Contemplation Stage:

If you are in this stage, you don’t have any intention to quit smoking in the near future (i.e., within the next 6 months). You feel that the benefits you receive from smoking outweigh the costs and risks of smoking. This is called the Pre-Contemplation Stage. If you are in this stage right now, you are not ready to use the patch.

Contemplation Stage:

After a period of time, often years, you may begin to realize that you are “hooked,” and that smoking is affecting your health and the health of those around you. You begin to think about the benefits of quitting, but you know that quitting will be difficult. You are seriously considering quitting smoking sometime within the next six months, but you are ambivalent. This is called the Contemplation Stage. In this stage, you may read articles on ways to quit or on the health effects of smoking, while you would have ignored this information in the Pre-Contemplation Stage. You begin to imagine your life without cigarettes. You also begin to experiment with making changes. For example, you may be trying to delay your first cigarette of the day, smoke only half of some cigarettes, or not smoke in your house or car. If you are in this stage right now, you are still not ready to use the patch.

Preparation Stage:

When you’ve made the decision to quit within the next month, and you have experimented with making changes, you’ve entered the Preparation Stage. Most people who have purchased the patch for the first time are in this stage. Preparation is a good name for this stage because thorough preparation greatly improves your chances of success. Just “winging it” or relying on willpower alone is not enough. You need a game plan that includes setting a quit date and committing to at least one person that you will make this change. Using this guide, as well as talking to the professionals at 1-888-HABITROL, will help you become fully prepared for your quit day and beyond.

Action Stage:

On the day that you quit smoking, you are in the Action Stage. It’s time to set your plan in motion. You will probably experience cravings for nicotine and urges to have a cigarette throughout the day, but through preparation, you have developed multiple strategies for dealing with your “triggers,” withdrawal symptoms and those cravings or urges to smoke. It’s important to start using the patch on the morning of your quit-day to help reduce urges to smoke and other withdrawal symptoms, such as irritability and difficulty concentrating.

Maintenance and Termination Stages:

If you are able to remain smoke-free for 6 months, you enter the Maintenance Stage. You like your new life, but still have occasional urges. Watch out for overconfidence. Thinking you can smoke “just one cigarette” should be a blinking neon warning sign. For most people, that one cigarette leads to two, then three, then full-time smoking again. Constantly remind yourself of the benefits you now enjoy as a nonsmoker. Have a plan ready to help you manage unexpected situations that may cause you stress and challenge your resolve to remain smoke-free. Most successful quitters will have occasional urges for many years.

Only about 1 in 5 quitters reach the Termination Stage, in which they have absolutely no temptation to smoke, and are 100% confident that they will never smoke again.

Your own chances to stop smoking depend on how strongly you are addicted to nicotine, how much you want to quit, and how closely you follow a quitting program like the one that comes with this product. If you find you cannot stop or if you start smoking again after using this product, please talk to a health care professional who can help you find a program that may work better for you.

the next 6 months). You feel that the benefits you receive from smoking outweigh the costs and risks of smoking. This is called the Pre-Contemplation Stage. If you are in this stage right now, you are not ready to use the patch.

the next 6 months). You feel that the benefits you receive from smoking outweigh the costs and risks of smoking. This is called the Pre-Contemplation Stage. If you are in this stage right now, you are not ready to use the patch.

Why I Want to Stop Smoking

Knowing that there are benefits to quitting is essential to your success. Writing down the reasons you want to quit on a card and keeping it with you to review can help you resist a temptation to smoke. Check off the reasons below that apply to you.

□ I want control back — I’m almost always thinking about or smoking a cigarette. I feel like the cigarette is controlling me.

□ I want to improve my chances of living a longer, healthier life.

□ I want to spend my cigarette money on other things — maybe a vacation.

□ I want more time for myself. Instead of taking those smoke breaks outside, I could be doing so many other things.

□ I want to look and smell better by getting rid of that lingering odor of smoke.

□ I want to set a healthier example for my children and grandchildren.

Write other reasons you have for quitting in the space below:

________________________________________________________

________________________________________________________

________________________________________________________

________________________________________________________

________________________________________________________

________________________________________________________

After completing this list, refer to it every day to reinforce your commitment to becoming a nonsmoker.

Health Benefits of Quitting

Most of us recognize the risks of smoking, such as cancer, heart disease and emphysema, but may not be aware of the many immediate and long-term benefits of quitting.

Immediate benefits in the first days and months may include:

• Breathing may get easier

• Food tastes better

• Sense of smell improves

• Walking and exercise may become easier

Remember, it’s never too late to quit. Whether you’re 34 or 84, your body can cleanse and start to repair the damage done by years of smoking.

Now that you are motivated and committed, the next step is to choose a quit date within the next 2–3 weeks to stop smoking. Decide whether it will be easier to quit on a workday when your smoking may already be restricted, or on the weekend when you are more relaxed. You may want to consider quitting at the beginning of the week, on a Sunday or Monday. It’s best to choose a date when:

• Your stress level is low

• You’ll be confronted with a minimum of smoking triggers

• You will not be in a social situation with other smokers, especially those that include alcohol

Enter your quit date on Day 1 of your Daily Success Calendar, located in the back of this guide.

Understanding Nicotine Addiction

Dependence on cigarettes is a twofold problem: the physical side of addiction to nicotine and the psychological side. Preparing to deal with both in advance will help make quitting easier and more comfortable.

Smoking and your body

As you know, smoking cigarettes is addictive. Nicotine, the addictive agent, reaches your brain in just seconds after each puff. Your brain and body get used to functioning with a certain level of nicotine. Within a few hours of your last cigarette, your nicotine level drops dramatically, resulting in withdrawal symptoms for most smokers.

Common withdrawal symptoms include intense cravings for nicotine, irritability, anxiety, depression, restlessness, difficulty concentrating, difficulty sleeping and increased appetite. Physical withdrawal symptoms usually peak within 24 to 72 hours after quitting, then decline over the next several weeks. Some smokers, however, may experience withdrawal symptoms for several months.

Staying on this patch for the full eight weeks can reduce the withdrawal symptoms you experience.

Smoking and your mind

The physical need for nicotine isn’t the only reason you may find it difficult to quit smoking. You can also be psychologically dependent.

Over time you’ve created strong associations or “triggers” to light up a cigarette. Sometimes you smoke for comfort: “Smoking helps me relax,” or “I don’t feel as angry when I smoke.” Sometimes it seems to make a social situation more enjoyable: “I like to smoke when I’m out having coffee with a friend or when drinking at a party.” At other times, you smoke out of habit: “I light up as soon as I get in the car,” “I smoke when I’m taking a break at work” or “Because I am so used to smoking, I feel uncomfortable without a cigarette in my hand.”

Knowing your “triggers”

Listed to the right are some of the common situations or activities that “trigger” smoking in many people and some suggestions on how to change your habits in order to reduce your urge to smoke.

Taming Your Triggers

Here are some other common “triggers.” Check off the ones that apply to you and write down how you will cope in the spaces below. Also, record other personal “triggers” and the things you plan to do instead.

Reducing the Urge to Smoke

Urges to smoke only last for a few seconds to a few minutes. Believe it or not, the urge to smoke will pass whether you smoke or not. When an urge strikes, try the following:

1. The “Three-Second Breathing” Exercise. Nothing relaxes you more quickly than taking a deep breath. Inhale deeply through pursed lips. Hold your breath for 3 seconds. Then slowly exhale through your mouth.

2. Switch your focus. Deliberately switch your attention from having a cigarette onto something else, like reading or stretching.
3. Use mental imagery to transform the urge into something manageable. For example, imagine the urge to smoke is like feeling thirsty. Then imagine reaching for a glass of cool ice water. Feel the coolness in your throat. Your entire body feels relief. You are calm and the urge has disappeared.

 | My Trigger; (In the past, I smoked ...) | My Solution; (Now, I will ...)
□ | To concentrate | _________________________________; _________________________________; _________________________________; _________________________________; _________________________________; _________________________________; _________________________________; _________________________________; _________________________________; _________________________________
□ | To relax | _________________________________; _________________________________; _________________________________; _________________________________; _________________________________; _________________________________; _________________________________; _________________________________; _________________________________; _________________________________
□ | To give myself a lift | _________________________________; _________________________________; _________________________________; _________________________________; _________________________________; _________________________________; _________________________________; _________________________________; _________________________________; _________________________________
□ | Because I was angry | _________________________________; _________________________________; _________________________________; _________________________________; _________________________________; _________________________________; _________________________________; _________________________________; _________________________________; _________________________________
□ | Because I was bored | _________________________________; _________________________________; _________________________________; _________________________________; _________________________________; _________________________________; _________________________________; _________________________________; _________________________________; _________________________________
□ | Because I felt stressed; _________________________________________; _________________________________________ | _________________________________; _________________________________; _________________________________; _________________________________; _________________________________; _________________________________; _________________________________; _________________________________; _________________________________; _________________________________

BOXED WARNING

Remember when you first tried a cigarette? Remember how awful it tasted? Remember your initial dizziness? Nausea? The point is, it took some time for you to learn how to smoke. Now you can learn not to smoke. That takes time too. Sticking with the HABITROL program can help. Call 1-888-HABITROL. We can help you develop customized solutions to your personal triggers.

Building Your Supporting Cast

Quitting isn’t easy. Sometimes you can feel all alone. This is where friends and family, both smokers and nonsmokers, can help. Take your friends and family through your quit plan. Once they understand why you are changing some of your old habits, they’ll be in a better position to understand and support you.

Tell your smoking friends of your desire to quit (truth is, many of them may have that same desire). You might be pleasantly surprised how supportive they can be. If your smoking friends express an interest in quitting, give them our number, 1-888-HABITROL, and we’ll help get them started. You might even choose to quit at the same time so that you can work as a team supporting one another.

It’s hard for people who have never smoked to understand what you’re going through, both emotionally and physically. Be patient with them. Explain that you might be a little (or very) irritable for a while.

Countdown to Quit Day — 10 Steps to Success

1. Tape a list of your reasons for quitting on the mirror. Go over them daily.

2. Tell one or two friends and your family. Ask for the specific help that you think you will need from each of them.

3. Use the HABITROL Take Control® Support Program.

4. Know your “triggers” and practice your coping strategies.

5. Change your routines (for example, sit in a different chair, not your smoking chair).

6. Plan how you will spend all the money you save from not smoking.

7. Freshen your environment. On the day before your quit date, clean your clothes, car and any rooms where you spend a lot of time.

8. Throw away any remaining cigarettes, ashtrays and lighters the night before your quit day.

9. Have plenty of low-calorie snacks available.

10. Use the patch as directed.

You should not smoke or use any other product containing nicotine while wearing the patch, since doing so will temporarily increase the level of nicotine in your blood. Furthermore, smoking even one cigarette reduces your chances of becoming smoke free.

Rewarding Yourself

Many people get this far and forget to reward themselves. We know that we are more likely to keep going if we get rewarded. So, in the space below, write ways that you can reward yourself at least once a day.

———————————————

———————————————

———————————————

———————————————

———————————————

———————————————

———————————————

If You Slip

Imagine that you go out with friends and end up having a cigarette. In other words, you “slipped.” This is not a relapse back to smoking. Don’t let this mistake make you feel like a failure or like giving up. Get back on track immediately. Don’t smoke another cigarette. Figure out why you had the slip and how, in the future, you will deal with the people, places or feelings that led to smoking. Do whatever works for you. The point is that slips, like mistakes, can be great learning experiences. If you slip and need help, give us a call at 1-888-HABITROL. We’ll be happy to help you find ways to cope — without a cigarette.

If you resume smoking

If you do return to your regular smoking habit, take some time to examine what went wrong. Did you quit without being prepared? Did you have and use the support of friends and family? If you are ready to try again, we can help you evaluate and revise your personal quit plan: call us at 1-888-HABITROL.

The patch helps smokers quit smoking by reducing nicotine withdrawal symptoms. Many patch users will be able to stop smoking for at least a few days, but many will start smoking again. Most smokers usually have to try to quit several times before they completely stop.

Your own chances to stop smoking depend on how strongly you are addicted to nicotine, how much you want to quit, and how closely you follow a quitting program like the one that comes with this product. If you find you cannot stop or if you start smoking again after using this product, please talk to a health care professional who can help you find a program that may work better for you.

And, if for some reason you are not ready to try again right now, keep these materials until you are ready. Before you set your quit date, call us to help you prepare for a successful quit.

A quick tip -- If you bought a pack of cigarettes to “just have one,” run the rest under cold water and then throw them out! Every single one! Don’t allow yourself to think that you can keep cigarettes stashed away and still resist them. Remember, the only reason to keep cigarettes around is to smoke them!

This product is only for those who want to stop smoking. The patch helps smokers quit by reducing nicotine withdrawal symptoms. Almost half of those who use this product will be able to stop smoking for at least a few days, but many will start smoking again. Most smokers will require several attempts before they stop smoking completely. Your own chances of quitting depend on how strongly you are addicted to nicotine, how motivated you are to quit, and how closely you follow a quit program, such as this one. If you find that you cannot stop smoking, or if you start smoking again after using the patch, talk with your doctor, who can help you find a program that may work better for you.

Do not use the patch if you continue to smoke, chew tobacco or use snuff, nicotine gum, nicotine nasal spray, nicotine inhaler or any other nicotine-containing product.

Ask your doctor before use if you:

• Have heart disease or an irregular heartbeat, or if you had a recent heart attack. Nicotine can increase your heart rate.

• Have high blood pressure not controlled with medication. Nicotine can increase blood pressure.

• Are allergic to any adhesives or patch ingredients or have skin problems, because you are more likely to get rashes.

• Are using a non-nicotine stop smoking drug.

• Take prescription medicine for depression or asthma. Your prescription dose may need to be adjusted.

Keep out of reach of children and pets. Used patches have enough nicotine to poison children and pets. If swallowed, get medical help or contact a Poison Control Center right away.

How the Patch Works

The patch is a nicotine transdermal system skin patch containing nicotine, the addictive agent in tobacco products. When you wear a patch, it gradually releases nicotine into your bloodstream through the skin. By replacing some of the nicotine to which your body has become accustomed from smoking, the patch helps reduce the nicotine withdrawal symptoms many people normally feel when they stop smoking. By offering three patches with different nicotine dose levels, this patch uses a step-down dosing system that allows you to gradually reduce your nicotine level by changing the patch you wear (moving to a lower dose) over an eight-week period. Nicotine replacement therapy can reduce nicotine withdrawal symptoms such as irritability, anxiety, restlessness, headaches, difficulty sleeping and concentrating, increased appetite, and craving for nicotine. By helping to reduce your physical nicotine withdrawal symptoms, the patch helps you to concentrate on the psychological aspects of quitting and to change your habits that “trigger” your nicotine cravings.

This patch program takes 8 weeks to complete, at the end of which you should stop using the patch. It is important that you keep using the patch until you have completed the entire program, and continue to use the HABITROL Take Control® Support Program when you need it.

It is important that you are firmly committed to giving up smoking.

Warnings:

• Have heart disease or an irregular heartbeat, or if you had a recent heart attack. Nicotine can increase

your heart rate.

• Have high blood pressure not controlled with medication. Nicotine can increase blood pressure.

• Are allergic to any adhesives or patch ingredients or have skin problems, because you are more likely

to get rashes.

• Are using a non-nicotine stop smoking drug.

• Take prescription medicine for depression or asthma. Your prescription dose may need to be adjusted.

Keep out of reach of children and pets. Used patches have enough nicotine to poison children and pets. If swallowed, get medical help or contact a Poison Control Center right away.

How the Patch Works

The patch is a nicotine transdermal system skin patch containing nicotine, the addictive agent in tobacco products. When you wear a patch, it gradually releases nicotine into your bloodstream through the skin. By replacing some of the nicotine to which your body has become accustomed from smoking, the patch helps reduce the nicotine withdrawal symptoms many people normally feel when they stop smoking. By offering three patches with different nicotine dose levels, this patch uses a step-down dosing system that allows you to gradually reduce your nicotine level by changing the patch you wear (moving to a lower dose) over an eight-week period. Nicotine replacement therapy can reduce nicotine withdrawal symptoms such as irritability, anxiety, restlessness, headaches, difficulty sleeping and concentrating, increased appetite, and craving for nicotine. By helping to reduce your physical nicotine withdrawal symptoms, the patch helps you to concentrate on the psychological aspects of quitting and to change your habits that “trigger” your nicotine cravings.

This patch program takes 8 weeks to complete, at the end of which you should stop using the patch. It is important that you keep using the patch until you have completed the entire program, and continue to use the HABITROL Take Control® Support Program when you need it.

Why wearing a nicotine patch isn’t as bad as smoking?

By placing a nicotine patch on your skin, you are NOT inhaling the harmful tars, toxins and chemicals found in cigarettes. These are the most dangerous parts of the cigarette.

And, because you’re not smoking while wearing the patch, there’s no second-hand smoke or odors to affect your family and friends.

How to Use the Patch

It is important that you are firmly committed to giving up smoking.

Warnings:

• If you are pregnant or breast-feeding, only use this medicine on the advice of your health care provider. Smoking can seriously harm your child. Try to stop smoking without using any nicotine replacement medicine. This medicine is believed to be safer than smoking. However, the risks to your child from this medicine are not fully known.

• Do not use if you continue to smoke, chew tobacco, use snuff, use nicotine gum, or use another nicotine patch or other nicotine containing products.

• Ask a doctor before use if you have heart disease, have had a recent heart attack, or have an irregular heartbeat. Nicotine can increase your heart rate.

• Ask a doctor before use if you have high blood pressure not controlled with medication. Nicotine can increase your blood pressure.

• Ask a doctor before use if you have an allergy to adhesive tape or have skin problems because you are more likely to get rashes with patch use.

• Ask a doctor or pharmacist before use if you are using a non-nicotine stop smoking drug.

• Ask a doctor or pharmacist before use if you are taking a prescription medicine for depression or asthma. Your prescription dose may need to be adjusted.

• When using this product, do not smoke even when not wearing the patch. The nicotine in your skin will still be entering your bloodstream for several hours after you take off the patch.

• When using this product, if you have vivid dreams or other sleep disturbances, you may remove the patch at bedtime and apply a new one in the morning.

• Stop use and ask a doctor if skin redness caused by the patch does not go away after four days, or if your skin swells, or you get a rash.

• Stop use and ask a doctor if irregular heartbeat or palpitations occur.

• Stop use and ask a doctor if you get symptoms of nicotine overdose, such as nausea, vomiting, dizziness, weakness and rapid heartbeat.

• Keep unused and used patches out of the reach of children and pets. Used patches have enough nicotine to poison children and pets. If swallowed, get medical help or contact a Poison Control Center right away. Save pouch to use for patch disposal. Dispose of the used patches by folding sticky ends together and putting in pouch. Do not wear more than one patch at a time.

• Do not cut the patch in half or into smaller pieces.

• Do not leave the patch on for more than 24 hours because it may irritate your skin and it loses strength after 24 hours.

• To avoid possible burns, remove patch before undergoing any MRI (Magnetic Resonance Imaging) procedures.

• Stop using the patch at the end of 8 weeks. The patch has been tested in 3 month studies and long

See chart on following page.

First, it is important that you are well prepared to give up smoking. If you are under 18 years of age, ask a doctor before use.

If you smoke 10 or less cigarettes per day:

• Do not use Step 1 Patch (21 mg/ day). Begin with Step 2 Patch (14mg/day) for 6 weeks, use Step 3 Patch (7mg/day) for 2 weeks and then stop.

• Steps 2 and 3 allow you to gradually reduce your level of nicotine. Completing the full program will increase your chance of quitting successfully.

• Stop at the end of eight weeks.

Lowering your patch dosage over 8 weeks will help you overcome your physical cravings for nicotine. You should talk to your doctor if, after you complete 8 weeks of patch use, you feel you need to continue therapy.

How to apply the Nicotine Transdermal System Patch

1. Choose a clean, dry, non hairy area of skin on your upper body or the outer part of your arm. Do not put a patch on skin that is very oily, burned, broken out, cut or irritated in any way. Immediately before applying the patch, wash your hands and the skin area with plain soap and water and dry completely. Avoid using any soap, lotion, hand cream, tanning lotion or oil, bath oil or insect repellent that contains aloe, lanolin or glycerin as a moisturizer. These products can leave a moisturizing film on your skin, which can interfere with the adherence of the patch.

2. Do not remove the patch from its sealed, protective pouch until you are ready to use it. Carefully cut open the child-resistant pouch along the dotted line, as indicated. If the new patch is cut, throw it away. Save pouch to use for patch disposal. Dispose of the used patches by folding sticky ends together and putting in pouch.

3. A shiny protective liner covers the sticky side of the patch where it contacts the skin. The liner has a precut slit to help you remove it from the patch. With the silver side facing you, pull the liner away from the patch, starting at the precut slit. Hold the patch at the edge (touch the sticky side as little as possible) and pull off the other piece of the protective liner. Throw this liner away.

4. Immediately apply the sticky side of the patch to your skin. Press the patch firmly against your skin with the palm of your hand for about 10 seconds. Make sure it sticks well to your skin, especially around the edges.

5. When you have finished applying or removing the patch, wash your hands with water only. Nicotine on your hands could get into your eyes and nose and could cause stinging, redness or irritation.

6. After 24 hours, remove the patch you have been wearing.

If you remove and apply the patch at about the same time each day, it will help you to remember when to put on a new patch. Choose a different place on your skin to apply the next patch and repeat steps 1 through 5. Do not reapply a patch to a previously used skin site for at least 1 week. Do not leave the patch on for more than 24 hours, because it may irritate your skin and loses strength after 24 hours. Do not wear more than one patch at the same time, and do not cut a patch in half or into smaller pieces to wear.

If you have trouble sleeping

You should wear the patch 24 hours a day. This may help overcome your morning cravings for nicotine. However, if you have vivid dreams or other sleep disturbances, you may remove the patch at bedtime and apply a new patch the following morning. The patch should be applied at approximately the same time each day.

If your patch comes off

If your patch falls off, put on a new one. Then remove this new patch at your regular time to keep your schedule the same. When applying the patch, be sure to press it firmly onto your skin with the palm of your hand for about 10 seconds, making sure that the patch sticks well, especially around the edges.

If your patch gets wet

Water will not harm or affect the patch you are wearing. You can take a bath or a shower, or you can swim while you are wearing the patch.

Disposing of the patch

Save pouch to use for patch disposal. Dispose of the used patches by folding sticky ends together and putting in pouch. Keep all used patches out of reach of children and pets.

Storage instructions

Keep the patch in its protective pouch until you are ready to use it. Store your patches between 20-25°C (68-77°F), because the patch is sensitive to heat. The inside of your car, for example, can reach much higher temperatures in the summer. Keep all unused patches out of the reach of children and pets.

If your skin reacts to the patch

When you first put on a patch, mild itching, burning, or tingling at the patch application site is normal and should go away within an hour. After you remove a patch, the skin under the patch might be somewhat red. Your skin should not stay red for more than a day. If you have a skin rash or redness caused by the patch that does not go away after 4 days, or your skin swells, call your doctor. Do not put on a new patch; you may be allergic to one of the components of the patch.

Other side effects you may experience

While wearing a nicotine replacement patch, you may experience one or more of the following side effects: nausea, dizziness, dry mouth, diarrhea, nervousness or restlessness, headache, vivid dreams or other sleep disturbances, and irritability.

If you experience any of the following side effects, immediately remove the patch and call your doctor:

• Severe skin irritation or discoloration

• Irregular heartbeats or palpitations

• Severe chest pain or tightening

• Symptoms of nicotine overdose, such as pallor (extreme paleness), cold sweat, nausea, abnormal salivation, vomiting, abdominal pain or severe headache, disturbed hearing or vision, dizziness, mental confusion or weakness.

It’s perfectly normal to gain some weight when you stop smoking. But don’t panic. Sometimes the weight change is simply a result of a change in your body’s metabolism. This is caused by your body’s withdrawal from nicotine. Your metabolism is simply returning to that of a nonsmoker. Besides, the average weight gain is only about five to ten pounds, and as you will see, there are things you can do to help control it.

Another source of extra pounds is the need for oral gratification. If you use food as a temporary substitute for cigarettes, you may gain weight. If you feel some concern about your weight, remember: a small weight gain is better than the high health risks associated with smoking.

The following tips will help you minimize the weight gain while you quit smoking.

How to control your weight by watching how and what you eat

Some general tips:

• Replace fattening snack foods with healthy, low-calorie snacks

• Keep low-fat, low-calorie snacks in the car

• Broil, boil, poach, or steam food instead of frying

• Remove fat from meat and skin from poultry

• Eat slowly and you’ll feel full sooner on less food

• Try eating several small meals a day instead of three big ones

• Drink a large glass of water before a meal

How to control your weight through the benefits of exercise

One of the best ways to control your weight is to move more. So if you already exercise regularly, keep it up. If not, start with small increases in your daily activity.

We’re NOT talking about running a marathon. We’re talking about walking to the corner store instead of hopping in the car. Or, walking up three flights of stairs instead of taking the elevator. Maybe you should rediscover your bicycle, take up golf or go for a swim.

A little exercise will do more than you think:

• It reduces possible weight gain while quitting smoking

•It can improve your sleeping

• It can make you feel better in general

• It reduces possible weight gain while quitting smoking

CHECK OFF EACH DAY AS A NONSMOKER AND

WATCH THOSE SUCCESSFUL DAYS ACCUMULATE

*If you smoke 10 or less cigarettes per day, start with the Step 2, 14 mg patch for 6 weeks, then step 3, 7 mg patch for 2 weeks.

CHECK OFF EACH DAY AS A NONSMOKER AND

WATCH THOSE SUCCESSFUL DAYS ACCUMULATE

Keep this card in your wallet, for easy access anytime.

(Side 1) (CREDIT CARD FLIP-OUT/Cut along dotted line

Nicotine Transdermal System

STOP SMOKING AID PATCH

HABITROL TAKE CONTROL SUPPORT PROGRAM® (with logo)

Call 1-888-HABITROL (1-888-422-4876)

Inactive ingredients

acrylate adhesive, aluminized polyester, cellulose paper, methacrylic acid copolymer

Comments or Questions?

Call 1-800-585-8682

Additional information

Habitrol Take Control Support Program® (with logo)

Nicotine Transdermal System Patch

STOP SMOKING AID

Includes: Behavior Support Program with self-help guide

TO INCREASE YOUR SUCCESS IN QUITTING:

1. You must be motivated to quit.
2. Use one patch daily according to directions.
3. Complete the full treatment program.
4. Do not use patch for more than 8 weeks.
5. Use patch with a behavioral support program, such as the one described in the enclosed booklet and on the compact disc.

Pouch Image:

Principal Display

NDC 54868-5821-0